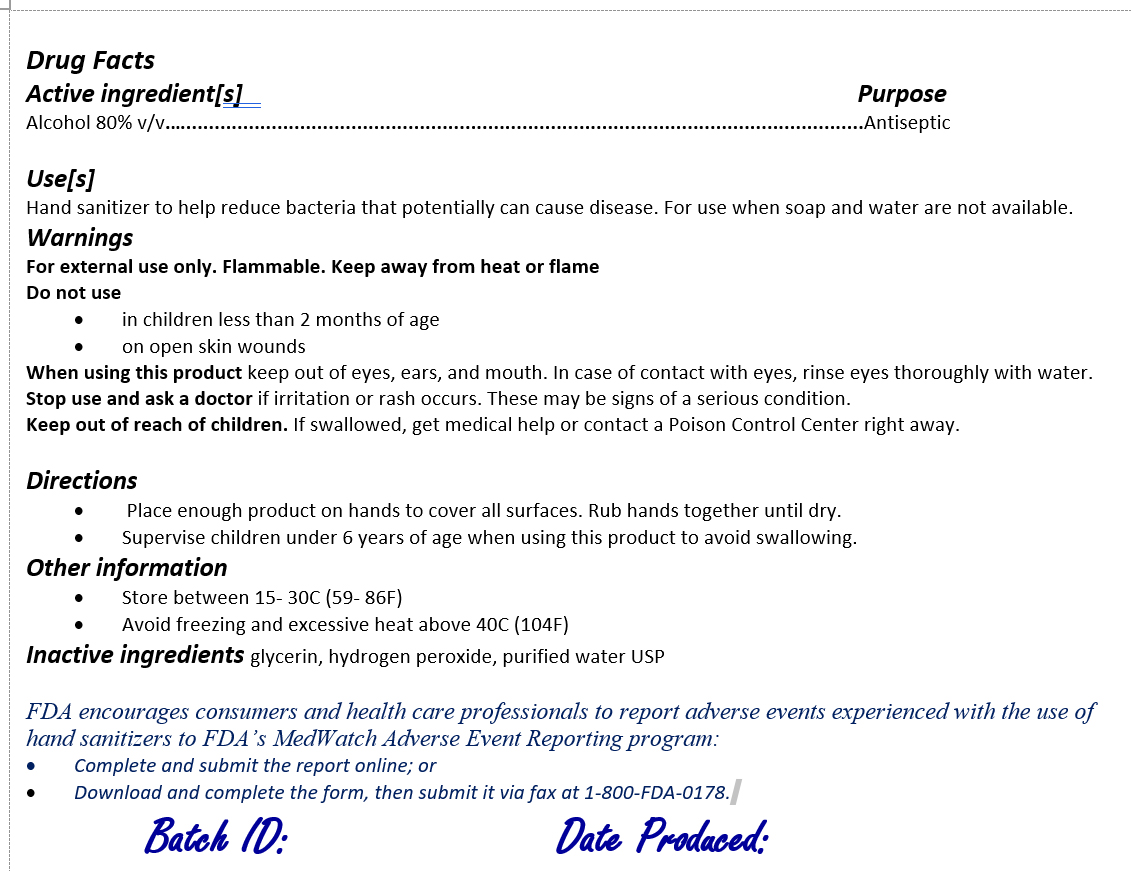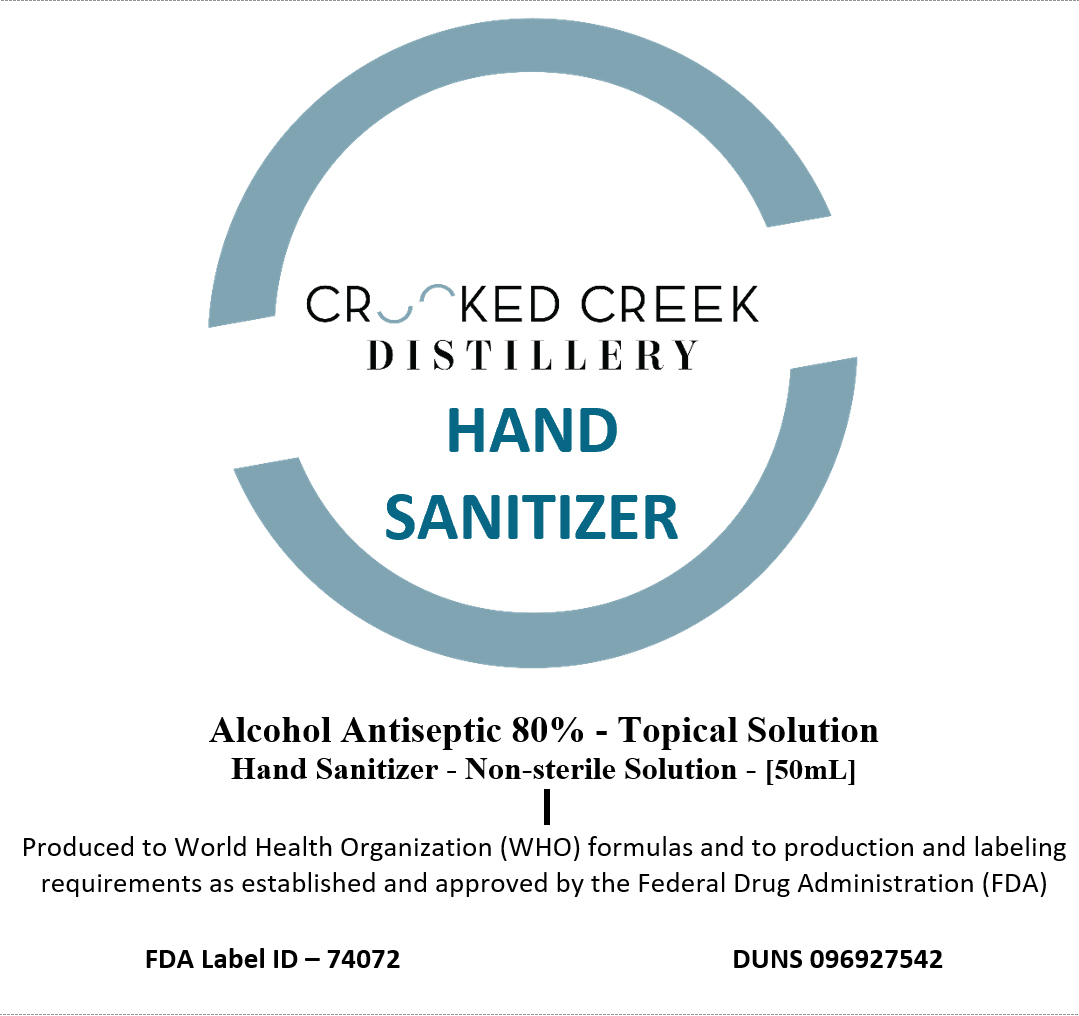 DRUG LABEL: Crooked Creek Distillery Inc Hand Sanitizer
NDC: 74072-100 | Form: LIQUID
Manufacturer: Crooked Creek Distillery Inc
Category: otc | Type: HUMAN OTC DRUG LABEL
Date: 20200325

ACTIVE INGREDIENTS: ALCOHOL 80 mL/100 mL
INACTIVE INGREDIENTS: HYDROGEN PEROXIDE 4.17 mL/100 mL

Front Label50ml

CROOKED CREEK DSITLLERY

HAND SANITIZER

Alcohol Antiseptic 80% - Topical Solution

Hand Sanitizer - Non-sterile Solution - [50mL]

Produced to World Health Organization (WHO) formulas and to production and labeling requirements as established and approved by the Federal Drug Administration (FDA)

FDA Label ID – 74072

DUNS 096927542

Back Label50ml

Drug Facts

Active ingredient[s] Purpose

Alcohol 80% v/v.….......................................................................................................................Antiseptic

Use[s]

Hand sanitizer to help reduce bacteria that potentially can cause disease. For use when soap and water are not available.

Warnings

For external use only. Flammable. Keep away from heat or flame

Do not use

in children less than 2 months of age
on open skin wounds

When using this product keep out of eyes, ears, and mouth. In case of contact with eyes, rinse eyes thoroughly with water.

Stop use and ask a doctor if irritation or rash occurs. These may be signs of a serious condition.

Keep out of reach of children. If swallowed, get medical help or contact a Poison Control Center right away.

Directions

Place enough product on hands to cover all surfaces. Rub hands together until dry.
Supervise children under 6 years of age when using this product to avoid swallowing.

Other information

Store between 15- 30C (59- 86F)
Avoid freezing and excessive heat above 40C (104F)

Inactive ingredients glycerin, hydrogen peroxide, purified water USP

FDA encourages consumers and health care professionals to report adverse events experienced with the use of hand sanitizers to FDA’s MedWatch Adverse Event Reporting program:

Complete and submit the report online; or
Download and complete the form, then submit it via fax at 1-800-FDA-0178.

Batch ID: Date Produced:

Purpose

Antiseptic

Active Ingredients

Active ingredient[s]
Alcohol 80% v/v

Warnings

For external use only. Flammable. Keep away from heat or flame

Do Not Use

in children less than 2 months of age
on open skin wounds

Stop use and ask a doctor if irritation or rash occurs. These may be signs of a serious condition.

Keep out of reach of children. If swallowed, get medical help or contact a Poison Control Center right away.

Inactive Ingredients

Inactive ingredients glycerin, hydrogen peroxide, purified water USP

Questions and Concerns

FDA encourages consumers and health care professionals to report adverse events experienced with the use of hand sanitizers to FDA’s MedWatch Adverse Event Reporting program:

Complete and submit the report online; or
Download and complete the form, then submit it via fax at 1-800-FDA-0178.

Batch Tracking and Production Date

Batch ID:

Date Produced:

Usage

Use[s]

Hand sanitizer to help reduce bacteria that potentially can cause disease. For use when soap and water are not available

When Using

When using this product keep out of eyes, ears, and mouth. In case of contact with eyes, rinse eyes thoroughly with water.

Indications and Usage

Use[s]

Hand sanitizer to help reduce bacteria that potentially can cause disease. For use when soap and water are not available.

When using this product keep out of eyes, ears, and mouth. In case of contact with eyes, rinse eyes thoroughly with water.

Directions

Place enough product on hands to cover all surfaces. Rub hands together until dry.

Directions

Place enough product on hands to cover all surfaces. Rub hands together until dry.
Supervise children under 6 years of age when using this product to avoid swallowing.

Storage

Other information

Store between 15- 30C (59- 86F)
Avoid freezing and excessive heat above 40C (104F)

Dosage and Administration

Directions

Place enough product on hands to cover all surfaces. Rub hands together until dry.
Supervise children under 6 years of age when using this product to avoid swallowing.

Other information

Store between 15- 30C (59- 86F)
Avoid freezing and excessive heat above 40C (104F)